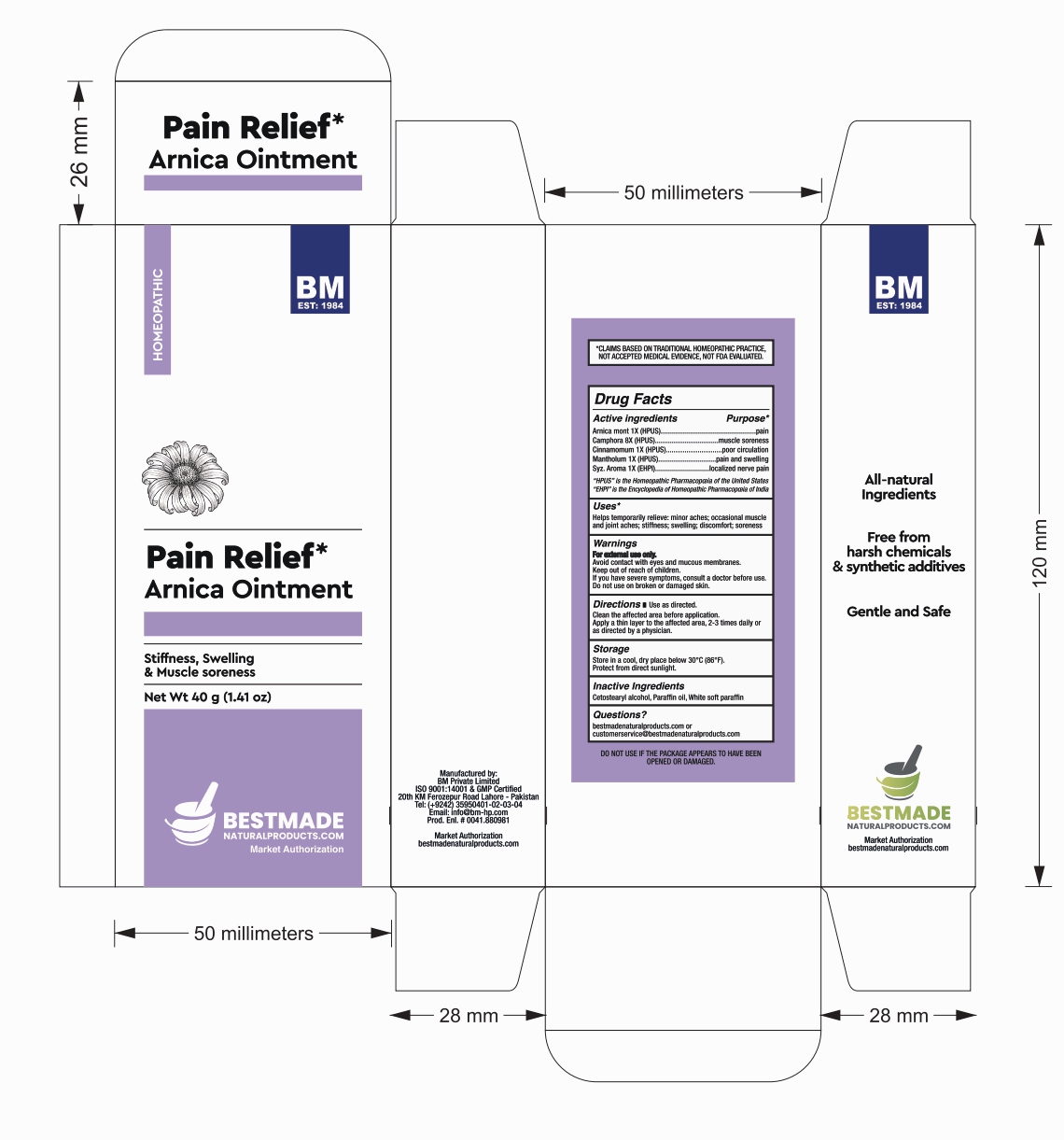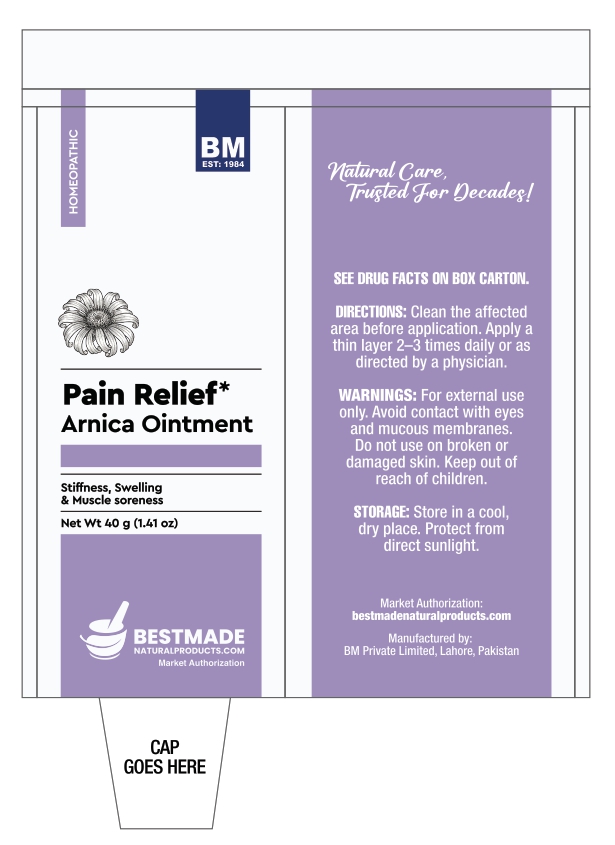 DRUG LABEL: BM Arnica
NDC: 85816-6029 | Form: OINTMENT
Manufacturer: BM Private Limited
Category: homeopathic | Type: HUMAN OTC DRUG LABEL
Date: 20251205

ACTIVE INGREDIENTS: CINNAMON OIL 1 [hp_X]/1 g; ARNICA MONTANA FLOWER 1 [hp_X]/1 g; CAMPHOR (NATURAL) 8 [hp_X]/1 g; CLOVE OIL 1 [hp_X]/1 g; MENTHOL, UNSPECIFIED FORM 1 [hp_X]/1 g
INACTIVE INGREDIENTS: WHITE PETROLATUM 0.815 g/1 g; MINERAL OIL 0.04 g/1 g; CETOSTEARYL ALCOHOL 0.095 g/1 g

BM Arnica Ointment

Active ingredients

Arnica mont 1X (HPUS)

Camphora 8X (HPUS)

Cinnamomum 1X (HPUS)

Mantholum 1X (HPUS)

Syz. Aroma 1X (EHPI)

Active ingredients Purpose*

Arnica mont 1X (HPUS)............pain

Camphora 8X (HPUS)..............muscle soreness

Cinnamomum 1X (HPUS)........poor circulation

Mantholum 1X (HPUS).............pain and swelling

Syz. Aroma 1X (EHPI)............localized nerve pain

Uses*

Helps temporarily relieve: minor aches; occasional muscle and joint aches; stiffness; swelling; discomfort; soreness

Warnings:

For external use only.

Avoid contact with eyes and mucous membranes.

Keep out of reach of children.

If you have severe symptoms, consult a doctor before use.

Do not use on broken or damaged skin.

Warnings:

Keep out of reach of children.

Directions:

Use as directed.

Clean the affected area before application.

Apply a thin layer to the affected area, 2-3 times daily or as directed by a physician.

Storage:

Store in a cool, dry place below 30°C (86°F).

Protect from direct sunlight.

Inactive Ingredients:

Cetostearyl alcohol, Paraffin oil, White soft paraffin

PACKAGE LABEL

Tube

Box